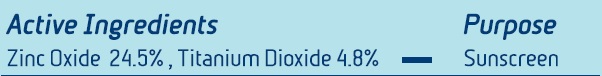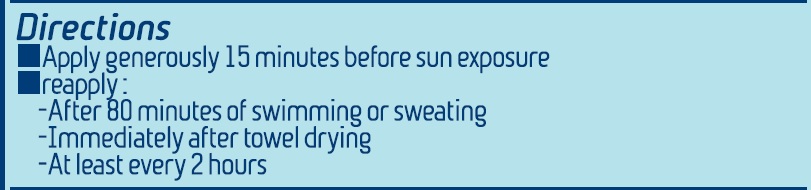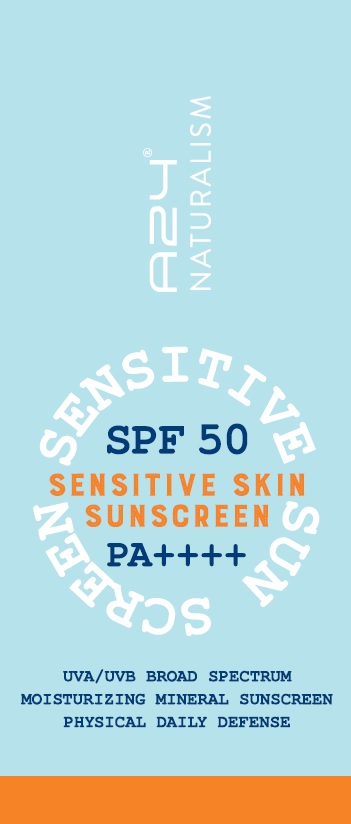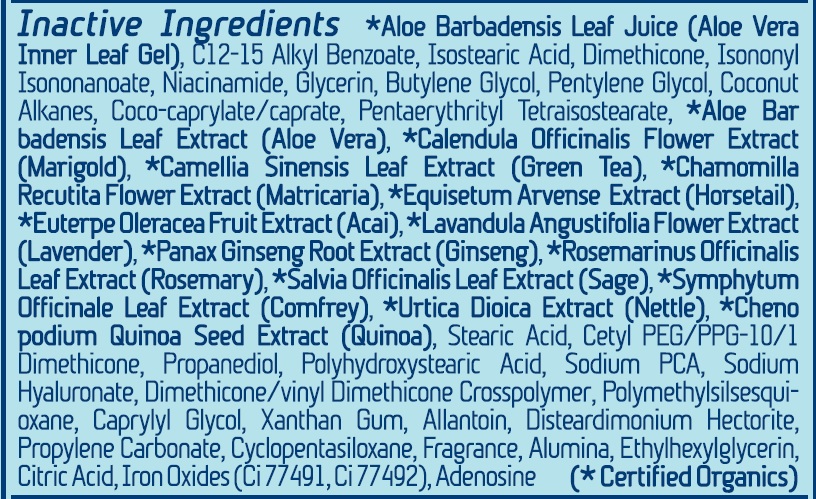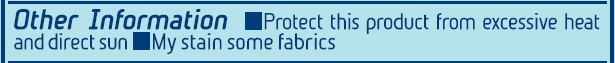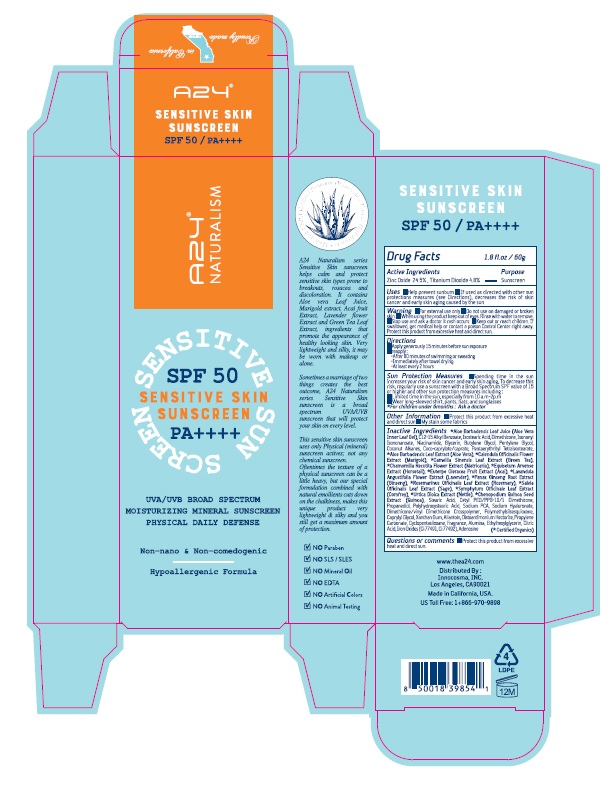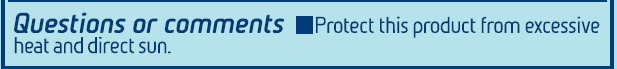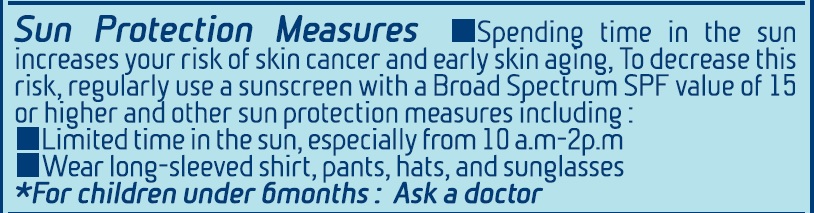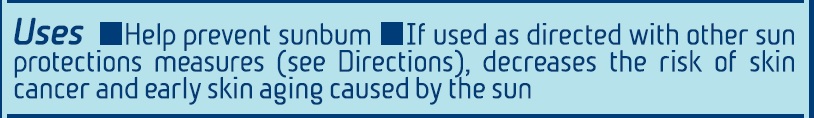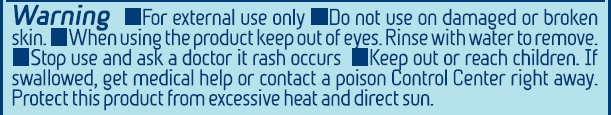 DRUG LABEL: A24 Naturalism Sensitive Skin Sunscreen SPF 50
NDC: 71331-109 | Form: CREAM
Manufacturer: Orange Lab
Category: otc | Type: HUMAN OTC DRUG LABEL
Date: 20230110

ACTIVE INGREDIENTS: TITANIUM DIOXIDE 2.88 g/60 g; ZINC OXIDE 14.7 g/60 g
INACTIVE INGREDIENTS: ADENOSINE; PROPANEDIOL; ALOE VERA LEAF; NIACINAMIDE; COCONUT ALKANES; COCO-CAPRYLATE/CAPRATE; ALUMINUM OXIDE; CALENDULA OFFICINALIS FLOWER; CAMELLIA SINENSIS FLOWER; MATRICARIA CHAMOMILLA LEAF; LAVANDULA ANGUSTIFOLIA FLOWER; ALKYL (C12-15) BENZOATE; ISOSTEARIC ACID; FERRIC OXIDE YELLOW; DISTEARDIMONIUM HECTORITE; PROPYLENE CARBONATE; CYCLOMETHICONE 5; EQUISETUM ARVENSE BRANCH; EUTERPE OLERACEA WHOLE; PANAX GINSENG ROOT OIL; SYMPHYTUM OFFICINALE WHOLE; CHENOPODIUM QUINOA SEED; STEARIC ACID; HYALURONATE SODIUM; POLYHYDROXYSTEARIC ACID (2300 MW); POLYMETHYLSILSESQUIOXANE (11 MICRONS); CAPRYLYL GLYCOL; XANTHAN GUM; BUTYLENE GLYCOL; ANHYDROUS CITRIC ACID; FERRIC OXIDE RED; ISONONYL ISONONANOATE; GLYCERIN; PENTYLENE GLYCOL; ROSEMARY; SALVIA OFFICINALIS WHOLE; PENTAERYTHRITYL TETRAISOSTEARATE; URTICA DIOICA LEAF; CETYL PEG/PPG-10/1 DIMETHICONE (HLB 2); ETHYLHEXYLGLYCERIN; DIMETHICONE 20; SODIUM PYRROLIDONE CARBOXYLATE; ALLANTOIN; DIMETHICONE/VINYL DIMETHICONE CROSSPOLYMER (SOFT PARTICLE)

A24 Naturalism Sensitive Skin Sunscreen SPF 50 PA++++